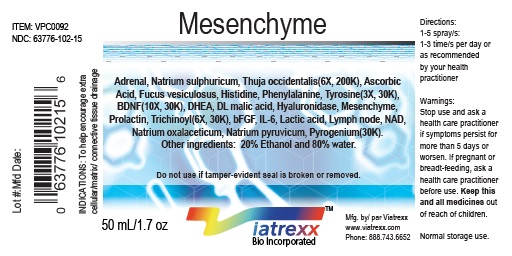 DRUG LABEL: Viatrexx-Mesenchyme
NDC: 63776-102 | Form: SPRAY
Manufacturer: VIATREXX BIO INCORPORATED
Category: homeopathic | Type: HUMAN OTC DRUG LABEL
Date: 20190319

ACTIVE INGREDIENTS: Bos Taurus Adrenal Gland 200 [kp_C]/1 mL; Sus Scrofa Adrenal Gland 200 [kp_C]/1 mL; Ascorbic Acid 30 [kp_C]/1 mL; Brain-Derived Neurotrophic Factor Human 30 [kp_C]/1 mL; Prasterone 30 [kp_C]/1 mL; Malic Acid 30 [kp_C]/1 mL; Basic Fibroblast Growth Factor (Human) 30 [kp_C]/1 mL; Fucus Vesiculosus 30 [kp_C]/1 mL; Histidine 30 [kp_C]/1 mL; Hyaluronidase 30 [kp_C]/1 mL; Human Interleukin-6 (Nonglycosylated) 30 [kp_C]/1 mL; Lactic Acid 30 [kp_C]/1 mL; Sus Scrofa Lymph Vessel 30 [kp_C]/1 mL; Bos Taurus Lymph Vessel 30 [kp_C]/1 mL; Sus Scrofa Mesenchyme 30 [kp_C]/1 mL; Nadide 30 [kp_C]/1 mL; Sodium Diethyl Oxalacetate 30 [kp_C]/1 mL; Sodium Pyruvate 30 [kp_C]/1 mL; Sodium Sulfate 200 [kp_C]/1 mL; Phenylalanine 30 [kp_C]/1 mL; Prolactin 30 [kp_C]/1 mL; Rancid Beef 30 [kp_C]/1 mL; Thuja Occidentalis Leaf 200 [kp_C]/1 mL; Dodecahydroxycyclohexane Dihydrate 30 [kp_C]/1 mL; Tyrosine 30 [kp_C]/1 mL
INACTIVE INGREDIENTS: Alcohol; Water

Mesenchyme

Active Ingredients

Adrenal (6X, 200K), Ascorbic acid (3X, 30K), BDNF (10X, 30K), DHEA (6X, 30K), Malic acid (6X, 30K), bFGF (30K), Fucus vesiculosus (3X 30K), Histidine (3X, 30K), Hyaluronidase (6X, 30K), IL-6 (30K), Lactic acid (30K), Lymph node (30K), Mesenchyme (6X, 30K), NAD (30K), Natrum oxalaceticum (30K), Natrum pyruvicum (30K), Natrum sulphuricum (6X, 200K), Phenylalanine (3X, 30K), Prolactin (6X, 30K), Pyrogenium (30K), Thuja occidentalis (6X, 200K), Trichinoyl (6X, 30K), Tyrosine (3X, 30K).

Purpose

Adrenal
Ascorbic acid
BDNF
DHEA
Malic acid
bFGF
Fucus vesiculosus
Histidine
Hyaluronidase
IL-6
Lactic acid
Lymph node
Mesenchyme
NAD
Natrum oxalaceticum
Natrum pyruvicum
Natrum sulphuricum
Phenylalanine
Prolactin
Pyrogenium
Thuja occidentalis
Trichinoyl
Tyrosine

Adrenal support
Anti-oxidant
Regeneration
Adrenal support
Cell respiration
Regeneration
Lymph support
Lg support
Tissue repair & regeneration
Inflammation & drainage
Cell respiration
Immune support
Regeneration
Cell respiration
Cell respiration
Cell respiration
Drainage
Amino Acid support
Endocrine & immune support
Drainage
Drainage
Immune support
Amino Acid support

Description

Viatrexx-Mesenchyme is a homeopathic product composed of physiological (low dose and low low dose) natural micro nutrients. These micro particles are designed to nourish the system.

Uses

To help encourage extra cellular / matrix / connective tissue drainage & support.

Warnings

Stop use and ask a health care practitioner if symptoms persist for more than five days or worsen. If pregnant or breastfeeding, ask a health care practitioner before use.

Dosage

1-3 spray(s); 1-3 time(s) per day or as recommended by your health care practitioner.

Inactive Ingredients

20% Alcohol and 80% Water

Product availability

Product may be acquired in 0.5, 30, 50, 100, 250 mL bottles.

References upon request

To report SUSPECTED ADVERSE REACTIONS, contact the FDA at 1-800-FDA-1088 or www.fda.gov/medwatch

Distributed by
Viatrexx Bio Incorporated
Newark, DE, USA, 19713

Manufactured by
8046255 Canada Inc
Beloeil, Qc, J3G 6S3
Date of last revision March 2019

For Questions and comments
Info@Viatrexx.com
www.Viatrexx.com

PACKAGE LABEL.PRINCIPAL DISPLAY PANEL

NDC: 63776-102-11
Item: VPC0092
Viatrexx Bio Incorporated
Viatrexx-Mesenchyme 0.5 mL ampule
For Oral and Topical Use
Expiry date: Lot #:
Manufactured for:
Viatrexx Bio Incorporated Newark, DE, USA, 19713
www.Viatrexx.com
Ingredients, homeopathic
See insert or www.viatrexx.com
Inactives: Alcohol 20%, Water 80%

NDC: 63776-102-14
Item: VPC0092
Viatrexx Bio Incorporated
Viatrexx-Mesenchyme 30 mL spray bottle
For Oral and Topical Use
Expiry date: Lot #:
Manufactured for:
Viatrexx Bio Incorporated Newark, DE, USA, 19713
www.Viatrexx.com
Ingredients, homeopathic
See insert or www.viatrexx.com
Inactives: Alcohol 20%, Water 80%

NDC: 63776-102-15
Item: VPC0092
Viatrexx Bio Incorporated
Viatrexx-Mesenchyme 50 mL spray bottle
For Oral and Topical Use
Expiry date: Lot #:
Manufactured for:
Viatrexx Bio Incorporated Newark, DE, USA, 19713
www.Viatrexx.com
Ingredients, homeopathic
See insert or www.viatrexx.com
Inactives: Alcohol 20%, Water 80%

NDC: 63776-102-16
Item: VPC0092
Viatrexx Bio Incorporated
Viatrexx-Mesenchyme 100 mL bottle
For Oral and Topical Use
Expiry date: Lot #:
Manufactured for:
Viatrexx Bio Incorporated Newark, DE, USA, 19713
www.Viatrexx.com
Ingredients, homeopathic
See insert or www.viatrexx.com
Inactives: Alcohol 20%, Water 80%

NDC: 63776-102-17
Item: VPC0092
Viatrexx Bio Incorporated
Viatrexx-Mesenchyme 250 mL bottle
For Oral and Topical Use
Expiry date: Lot #:
Manufactured for:
Viatrexx Bio Incorporated Newark, DE, USA, 19713
www.Viatrexx.com
Ingredients, homeopathic
See insert or www.viatrexx.com
Inactives: Alcohol 20%, Water 80%